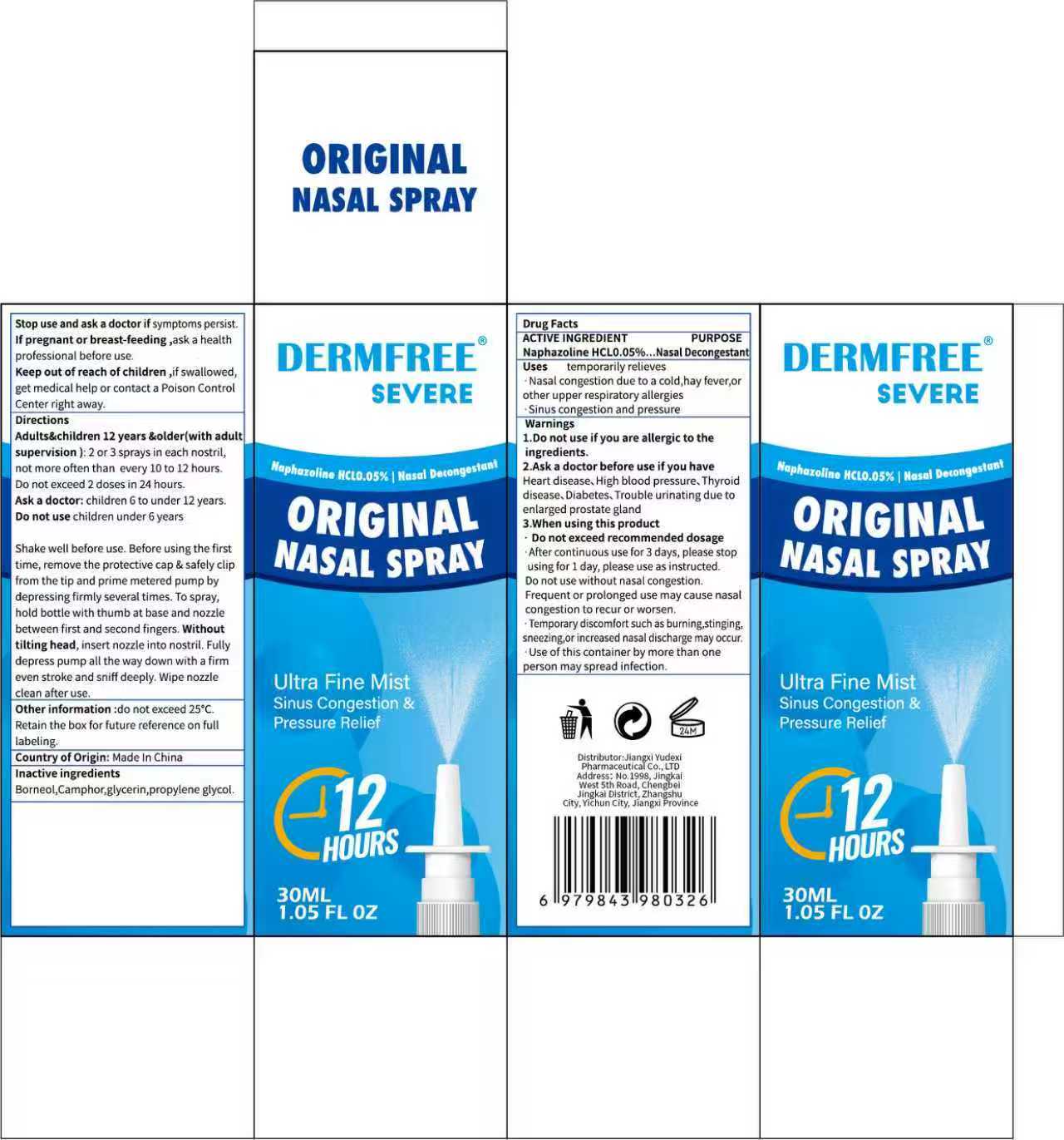 DRUG LABEL: DERMFREE ORIGINAL NASAL
NDC: 85248-112 | Form: SPRAY
Manufacturer: Jiangxi Yudexi Pharmaceutical Co., LTD
Category: otc | Type: HUMAN OTC DRUG LABEL
Date: 20260208

ACTIVE INGREDIENTS: NAPHAZOLINE HCL 0.05 g/100 mL
INACTIVE INGREDIENTS: BORNEOL; GLYCERIN; PROPYLENE GLYCOL; CAMPHOR (SYNTHETIC)

85248-112

Active Ingredient

Naphazoline HCL 0.05%.

Purpose

Nasal Decongestant

Use

temporarily relieves .Nasal congestion due to a cold, hay fever, or other upper respiratory allergies .Sinus congestion and pressure

Warnings

1.Do not use if you are allergic to the ingredients. 2.Ask a doctor before use if you have Heart disease、High blood pressure、Thyroid disease、Diabetes、Trouble urinating due to enlarged prostate gland 3.When using this product
Do not exceed recommended dosage

Do not use if you are allergic to the ingredients.
Do not use without nasal congestion. Do not use:children under 6 years.

When Using

·Do not exceed recommended dosage.
·After continuous use for 3 days, please stopusing for 1 day, please use as instructed.Do not use without nasal congestion.Frequent or prolonged use may cause nasal
congestion to recur or worsen.
·Temporary discomfort such as burning,stinging,sneezing,or increased nasal discharge may occur.
·Use of this container by more than one person may spread infection.

Stop Use

Stop use and ask a doctor if symptoms persist.
If pregnant or breast-feeding ,ask a healthprofessional before use.

Ask Doctor

Stop use and ask a doctor if symptoms persist.
If pregnant or breast-feeding ,ask a health professional before use.
Ask a doctor before use if you have
Heart disease, High blood pressure, Thyroiddisease, Diabetes, Trouble urinating due toenlarged prostate gland.
Ask a doctor :children 6 to under 12 years.

Keep Oot Of Reach Of Children

if swallowed, get medical help or contact a Poison Control Center right away.

Directions

Adults&children 12 years &older(with adult supervision):2 or 3 sprays in each nostril,not more often than every 10 to 12 hours.Do not exceed 2 doses in 24 hours.Ask a doctor: children 6 to under 12 years.Do not use children under 6 years.
Shake well before use. Before using the first time, remove the protective cap & safely clip from the tip and prime metered pump by depressing firmly several times. To spray,hold bottle with thumb at base and nozzle between first and second fingers. Without tilting head, insert nozzle into nostril. Fully depress pump all the way down with a firmeven stroke and sniff deeply. Wipe nozzle clean after use

Other information

do not exceed 25°C.Retain the box for future reference on full labeling.
Country of Origin: Made In China

Inactive ingredients

Borneol,Camphor,glycerin,propylene glycol